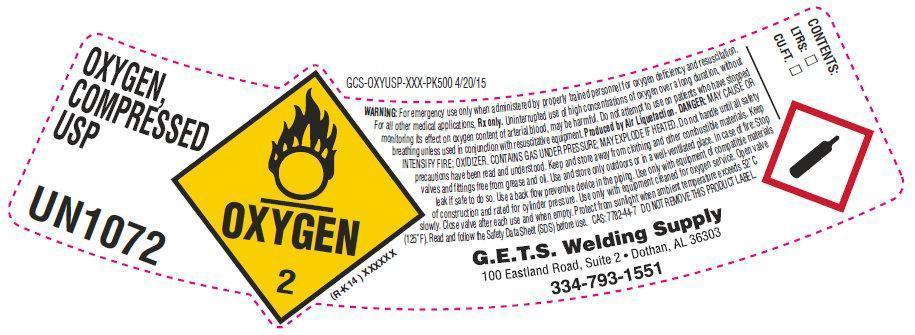 DRUG LABEL: OXYGEN
NDC: 69878-001 | Form: GAS
Manufacturer: Gases Equipment Tools and Supplies Inc
Category: prescription | Type: HUMAN PRESCRIPTION DRUG LABEL
Date: 20221101

ACTIVE INGREDIENTS: OXYGEN 992 mL/1 L

OXYGEN